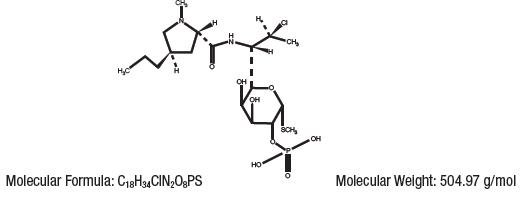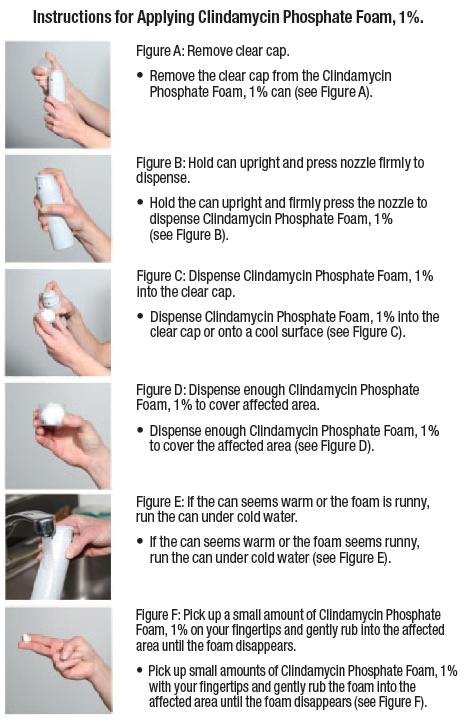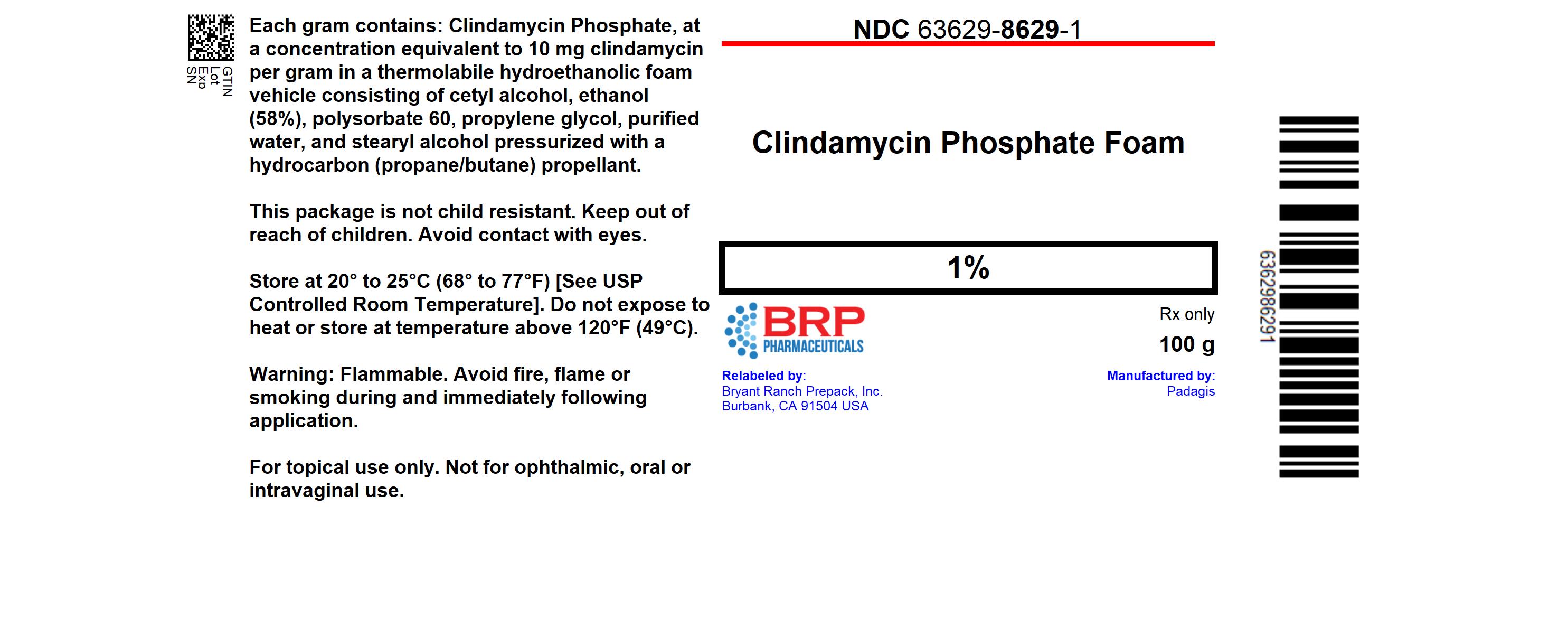 DRUG LABEL: Clindamycin Phosphate
NDC: 63629-8629 | Form: AEROSOL, FOAM
Manufacturer: Bryant Ranch Prepack
Category: prescription | Type: HUMAN PRESCRIPTION DRUG LABEL
Date: 20230717

ACTIVE INGREDIENTS: CLINDAMYCIN PHOSPHATE 10 mg/1 g
INACTIVE INGREDIENTS: ALCOHOL; POLYSORBATE 60; PROPYLENE GLYCOL; WATER; STEARYL ALCOHOL; CETYL ALCOHOL

HIGHLIGHTS OF PRESCRIBING INFORMATION

These highlights do not include all the information needed to use Clindamycin Phosphate Foam, 1% safely and effectively. See full prescribing information for Clindamycin Phosphate Foam, 1%.
Clindamycin Phosphate Foam, 1%
For Topical Use
Initial U.S. Approval: 1970

1 INDICATIONS AND USAGE

Clindamycin Phosphate Foam, 1% is a lincosamide product indicated for acne vulgaris in patients 12 years and older. (1)

2 DOSAGE AND ADMINISTRATION

- For topical use only; not for oral, ophthalmic, or intravaginal use. (2)
- Apply Clindamycin Phosphate Foam, 1% once daily to affected areas. (2)
- Flammable; avoid fire, flame and/or smoking during and immediately following application. (2)

3 DOSAGE FORMS AND STRENGTHS

Foam containing 1% clindamycin as clindamycin phosphate. (3)

4 CONTRAINDICATIONS

Clindamycin Phosphate Foam, 1% is contraindicated in individuals with a history of regional enteritis or ulcerative colitis, or a history of antibiotic-associated colitis, (including pseudomembranous colitis). (4)

5 WARNINGS AND PRECAUTIONS

- Colitis: Clindamycin can cause severe colitis, which may result in death. Diarrhea, bloody diarrhea, and colitis (including pseudomembranous colitis) have been reported with the use of clindamycin. Clindamycin Phosphate Foam, 1% should be discontinued if significant diarrhea occurs. (5.1)

6 ADVERSE REACTIONS

The most common adverse reactions (>1%) are headache and application site reactions including burning, pruritus, and dryness. (6.1)

To report SUSPECTED ADVERSE REACTIONS, contact Perrigo at 1-866-634-9120 or FDA at 1-800-FDA-1088 or www.fda.gov/medwatch.

FULL PRESCRIBING INFORMATION

1 INDICATIONS AND USAGE

Clindamycin Phosphate Foam, 1% is indicated for topical application in the treatment of acne vulgaris in patients 12 years and older.

2 DOSAGE AND ADMINISTRATION

Clindamycin Phosphate Foam, 1% is for topical use only, and not for oral, ophthalmic or intravaginal use.

Apply Clindamycin Phosphate Foam, 1% once daily to affected areas after the skin is washed with mild soap and allowed to fully dry. Use enough to cover the entire affected area.

If there has been no improvement after 6 to 8 weeks or if the condition becomes worse, treatment should be discontinued.

The contents of Clindamycin Phosphate Foam, 1% are flammable; avoid fire, flame and/or smoking during and immediately following application.

3 DOSAGE FORMS AND STRENGTHS

White to off-white thermolabile foam. Each gram of Clindamycin Phosphate Foam, 1% contains, as dispensed, 12 mg (1.2%) of clindamycin phosphate, equivalent to 10 mg (1%) of clindamycin.

4 CONTRAINDICATIONS

Clindamycin Phosphate Foam, 1% is contraindicated in individuals with a history of regional enteritis or ulcerative colitis, or a history of antibiotic-associated colitis (including pseudomembranous colitis).

5 WARNINGS AND PRECAUTIONS

5.1 Colitis

Systemic absorption of clindamycin has been demonstrated following topical use of this product. Diarrhea, bloody diarrhea, and colitis (including pseudomembranous colitis) have been reported with the use of topical clindamycin. If significant diarrhea occurs, Clindamycin Phosphate Foam, 1% should be discontinued. [ See Adverse Reactions(6.2). ]

Severe colitis has occurred following oral or parenteral administration of clindamycin with an onset of up to several weeks following cessation of therapy. Antiperistaltic agents such as opiates and diphenoxylate with atropine may prolong and/or worsen severe colitis. Severe colitis may result in death.

Studies indicate a toxin(s) produced by Clostridiais one primary cause of antibiotic-associated colitis. The colitis is usually characterized by severe persistent diarrhea and severe abdominal cramps and may be associated with the passage of blood and mucus. Stool cultures for Clostridium difficileand stool assay for C. difficiletoxin may be helpful diagnostically.

5.2 Irritation

Clindamycin Phosphate Foam, 1% can cause irritation. Concomitant topical acne therapy should be used with caution since a possible cumulative irritancy effect may occur, especially with the use of peeling, desquamating, or abrasive agents. If irritation or dermatitis occurs, clindamycin should be discontinued.

Avoid contact of Clindamycin Phosphate Foam, 1% with eyes, mouth, lips, other mucous membranes or areas of broken skin. If contact occurs, rinse thoroughly with water.

Clindamycin Phosphate Foam, 1% should be prescribed with caution in atopic individuals.

6 ADVERSE REACTIONS

6.1 Clinical Trials Experience

Because clinical trials are conducted under widely varying conditions, adverse reaction rates observed in the clinical trials of a drug cannot be directly compared to rates in the clinical trials of another drug and may not reflect the rates observed in clinical practice.

A total of 439 subjects with mild to moderate acne vulgaris were treated once daily for 12 weeks with clindamycin phosphate foam, 1%.

The incidence of adverse reactions occurring in >1% of the subjects in clinical trials comparing clindamycin phosphate foam, 1% and its vehicle is presented in Table 1.

Table 1: Adverse Reactions Occurring in ≥ 1% of Subjects

Adverse Reactions | Number (%) of Subjects
 | Clindamycin Phosphate Foam, 1%; N = 439 | Vehicle Foam; N = 154
Headache | 12 (3%) | 1 (1%)
Application site burning | 27 (6%) | 14 (9%)
Application site pruritus | 5 (1%) | 5 (3%)
Application site dryness | 4 (1%) | 5 (3%)
Application site reaction, not otherwise specified | 3 (1%) | 4 (3%)

In a contact sensitization study, none of the 203 subjects developed evidence of allergic contact sensitization to clindamycin phosphate foam, 1%.

6.2 Postmarketing Experience

The following adverse reactions have been identified during post approval use of clindamycin phosphate foam, 1%: application site pain, application site erythema, diarrhea, urticaria, abdominal pain, hypersensitivity, rash, abdominal discomfort, nausea, seborrhea, application site rash, dizziness, pain of skin, colitis (including pseudomembranous colitis), and hemorrhagic diarrhea. Because these reactions are reported voluntarily from a population of uncertain size, it is not always possible to reliably estimate their frequency or establish a causal relationship to drug exposure.

Abdominal pain and gastrointestinal disturbances, as well as gram-negative folliculitis, have also been reported in association with the use of topical formulations of clindamycin. Orally and parenterally administered clindamycin have been associated with severe colitis, which may end fatally.

7 DRUG INTERACTIONS

7.1 Erythromycin

Clindamycin Phosphate Foam, 1% should not be used in combination with topical or oral erythromycin-containing products due to possible antagonism to its clindamycin component. In vitrostudies have shown antagonism between these two antimicrobials. The clinical significance of this in vitroantagonism is not known.

7.2 Neuromuscular Blocking Agents

Clindamycin has been shown to have neuromuscular blocking properties that may enhance the action of other neuromuscular blocking agents. Therefore, Clindamycin Phosphate Foam, 1% should be used with caution in patients receiving such agents.

8 USE IN SPECIFIC POPULATIONS

8.1 Pregnancy

Pregnancy Category B: There are no adequate and well-controlled studies in pregnant women treated with clindamycin phosphate foam, 1%. Clindamycin Phosphate Foam, 1% should be used during pregnancy only if the potential benefit clearly outweighs the potential risk to the fetus.

Reproduction studies have been performed in rats and mice using subcutaneous and oral doses of clindamycin phosphate, clindamycin hydrochloride and clindamycin palmitate hydrochloride. These studies revealed no evidence of fetal harm.

The highest dose used in the rat and mouse teratogenicity studies was equivalent to a clindamycin phosphate dose of 432 mg/kg. For a rat, this dose is 84 fold higher, and for a mouse 42 fold higher, than the anticipated human dose of clindamycin phosphate from clindamycin phosphate foam, 1% based on a mg/m^2comparison.

8.3 Nursing Mothers

It is not known whether clindamycin is excreted in human milk following use of Clindamycin Phosphate Foam, 1%. However, orally and parenterally administered clindamycin has been reported to appear in breast milk. Because of the potential for serious adverse reactions in nursing infants, a decision should be made whether to discontinue nursing or to discontinue the drug, taking into account the importance of the drug to the mother.

If used during lactation and Clindamycin Phosphate Foam, 1% is applied to the chest, care should be taken to avoid accidental ingestion by the infant.

8.4 Pediatric Use

Safety and effectiveness of clindamycin phosphate foam, 1% in children under the age of 12 have not been studied.

8.5 Geriatric Use

The clinical study with clindamycin phosphate foam, 1% did not include sufficient numbers of subjects aged 65 and over to determine if they respond differently than younger subjects.

11 DESCRIPTION

Clindamycin Phosphate Foam, 1% contains clindamycin (1%) as clindamycin phosphate.

Clindamycin phosphate is a water-soluble ester of the semi-synthetic antibiotic produced by a 7(S)-chloro-substitution of the 7(R)-hydroxyl group of the parent antibiotic, lincomycin.

The chemical name for clindamycin phosphate is methyl 7-chloro-6,7,8-trideoxy-6-(1-methyl- trans-4-propyl-L-2-pyrrolidinecarboxamido)1-thio-L- threo-α-D- galacto- octopyranoside 2-(dihydrogen phosphate). The structural formula for clindamycin phosphate is represented below:

Clindamycin Phosphate Foam, 1% contains clindamycin (1%) as clindamycin phosphate, at a concentration equivalent to 10 mg clindamycin per gram in a thermolabile hydroethanolic foam vehicle consisting of cetyl alcohol, ethanol (58%), polysorbate 60, propylene glycol, purified water, and stearyl alcohol pressurized with a hydrocarbon (propane/butane) propellant.

12 CLINICAL PHARMACOLOGY

12.1 Mechanism of Action

Mechanism of action in acne vulgaris is unknown. [ See Microbiology (12.4)]

12.2 Pharmacodynamics

Pharmacodynamics of Clindamycin Phosphate Foam, 1% is unknown.

12.3 Pharmacokinetics

In an open label, parallel group study in 24 subjects with acne vulgaris, 12 subjects (3 male and 9 female) applied 4 grams of clindamycin phosphate foam, 1% once-daily for five days, and 12 subjects (7 male and 5 female) applied 4 grams of a clindamycin gel, 1%, once daily for five days. On Day 5, the mean Cmaxand AUC(0-12)were 23% and 9% lower, respectively, for clindamycin phosphate foam, 1% than for the clindamycin gel, 1%.

Following multiple applications of clindamycin phosphate foam, 1%, less than 0.024% of the total dose was excreted unchanged in the urine over 12 hours on Day 5.

12.4 Microbiology

No microbiology studies were conducted in the clinical trials with this product.

Clindamycin binds to the 50S ribosomal subunits of susceptible bacteria and prevents elongation of peptide chains by interfering with peptidyl transfer, thereby suppressing protein synthesis. Clindamycin has been shown to have in vitroactivity against Propionibacterium acnes(P. acnes), an organism that has been associated with acne vulgaris; however, the clinical significance of this activity against P. acneswas not examined in clinical studies with Clindamycin Phosphate Foam, 1%. P. acnesresistance to clindamycin has been documented.

Inducible Clindamycin Resistance

The treatment of acne with antimicrobials is associated with the development of antimicrobial resistance in P. acnesas well as other bacteria (e.g. Staphylococcus aureus, Streptococcus pyogenes). The use of clindamycin may result in developing inducible resistance in these organisms. This resistance is not detected by routine susceptibility testing.

Cross Resistance

Resistance to clindamycin is often associated with resistance to erythromycin.

13 NONCLINICAL TOXICOLOGY

13.1 Carcinogenesis, Mutagenesis, Impairment of Fertility

The carcinogenicity of a 1.2% clindamycin phosphate gel similar to Clindamycin Phosphate Foam, 1% was evaluated by daily application to mice for two years. The daily doses used in this study were approximately 3 and 15 times higher than the human dose of clindamycin phosphate from 5 milliliters of Clindamycin Phosphate Foam, 1%, assuming complete absorption and based on a body surface area comparison. No significant increase in tumors was noted in the treated animals.

A 1.2% clindamycin phosphate gel similar to Clindamycin Phosphate Foam, 1% caused a statistically significant shortening of the median time to tumor onset in a study in hairless mice in which tumors were induced by exposure to simulated sunlight.

Genotoxicity tests performed included a rat micronucleus test and an Ames Salmonella reversion test. Both tests were negative.

Reproduction studies in rats using oral doses of clindamycin hydrochloride and clindamycin palmitate hydrochloride have revealed no evidence of impaired fertility.

14 CLINICAL STUDIES

In one multicenter, randomized, double-blind, vehicle-controlled clinical trial, subjects with mild to moderate acne vulgaris used clindamycin phosphate foam, 1% or the vehicle Foam once daily for twelve weeks. Treatment response, defined as the proportion of subjects clear or almost clear, based on the Investigator Static Global Assessment (ISGA), and the mean percent reductions in lesion counts at the end of treatment in this study are shown in Table 2.

Table 2: Efficacy Results at Week 12

Efficacy Parameters | Clindamycin Phosphate Foam, 1%; N = 386 | Vehicle Foam; N = 127
Treatment response (ISGA) | 31% | 18%*
Percent reduction in lesion counts
Inflammatory Lesions | 49% | 35%*
Noninflammatory Lesions | 38% | 27%*
Total Lesions | 43% | 31%*

*P<0.05

16 HOW SUPPLIED/STORAGE AND HANDLING

16.1 How Supplied
Clindamycin Phosphate Foam, 1% containing clindamycin phosphate equivalent to 10 mg clindamycin per gram, is white to off-white in color and thermolabile.

It is available in the following sizes:

- 100 gram aerosol can - NDC 63629-8629-1

16.2 Storage and Handling
Store at 20-25°C (68-77°F) [see USP controlled room temperature].

Flammable. Avoid fire, flame or smoking during and immediately following application.

Contents under pressure. Do not puncture or incinerate. Do not expose to heat or store at temperature above 120°F (49°C).

Keep out of reach of children.

17 PATIENT COUNSELING INFORMATION

See FDA-Approved patient labeling (Patient Information).

17.1 Instructions for Use

- Patients should be advised to wash their skin with mild soap and allow it to dry before applying Clindamycin Phosphate Foam, 1%.
- Patients should use enough Clindamycin Phosphate Foam, 1% to cover the face and to apply once daily.
- Patients should dispense Clindamycin Phosphate Foam, 1% directly into the cap or onto a cool surface.

Patients should wash their hands after applying Clindamycin Phosphate Foam, 1%.

17.2 Skin Irritation

Clindamycin Phosphate Foam, 1% may cause irritation such as erythema, scaling, itching, burning, or stinging. Patients should be advised to discontinue use if excessive irritancy or dermatitis occur.

17.3 Colitis

In the event a patient treated with Clindamycin Phosphate Foam, 1% experiences severe diarrhea or gastrointestinal discomfort, Clindamycin Phosphate Foam, 1% should be discontinued and a physician should be contacted.

Made in Israel

Manufactured by Perrigo

Yeruham, Israel

Distributed by Perrigo

Allegan, MI 49010

www.perrigo.com

Rev 08-19

4T500 RC J4

Pharmacist-Detach here and Give Instructions to Patient

Patient Information

Clindamycin Phosphate Foam, 1%

Important: For skin use only. Do not use Clindamycin Phosphate Foam, 1% in your eyes, mouth or vagina.

Read the Patient Information that comes with Clindamycin Phosphate Foam, 1% before you start using it and each time you get a refill. There may be new information. This leaflet does not take the place of talking with your doctor about your medical condition or treatment.

What is Clindamycin Phosphate Foam, 1%?

Clindamycin Phosphate Foam, 1% is a prescription medicine used on the skin (topical) to treat acne in people 12 years and older.

It is not known if Clindamycin Phosphate Foam, 1% is safe and effective in children under 12 years of age.

Who should not use Clindamycin Phosphate Foam, 1%?

Do not use Clindamycin Phosphate Foam, 1% if you:

- have Crohn’s disease
- have ulcerative colitis
- have had inflammation of the colon (colitis) or severe diarrhea with past antibiotic use

Tell your doctor if you are not sure if you have anyof the conditions listed above.

What should I tell my doctor before using Clindamycin Phosphate Foam, 1%? Before you use Clindamycin Phosphate Foam, 1%, tell your doctor if you:

- have a history of eczema
- are planning to have surgery. Clindamycin Phosphate Foam, 1% may affect how certain medicines work that may be given during surgery.
- have any other medical conditions
- are pregnant or planning to become pregnant. It is not known if Clindamycin Phosphate Foam, 1% may harm your unborn baby.
- are breastfeeding or plan to breastfeed. It is not known if Clindamycin Phosphate Foam, 1% passes through your breast milk.

You and your doctor should decide if you will use Clindamycin Phosphate Foam, 1% or breastfeed. If you use Clindamycin Phosphate Foam, 1% while breastfeeding and Clindamycin Phosphate Foam, 1% is applied on the chest, take care to avoid getting Clindamycin Phosphate Foam, 1% into your baby’s mouth.

Tell your doctor about all the medicines you takeincluding prescription and non-prescription medicines, vitamins and herbal supplements. Clindamycin Phosphate Foam, 1% may affect the way other medicines work and other medicines may affect how Clindamycin Phosphate Foam, 1% works.

Especially tell your doctor if you take erythromycin or use products on your skin that contain erythromycin.

Know the medicines you take. Keep a list of them to show your doctor and pharmacist when you get a new medicine.

How should I use Clindamycin Phosphate Foam, 1%?

- Clindamycin Phosphate Foam, 1% is for use on the skin only. Do not get Clindamycin Phosphate Foam, 1% in your eyes, mouth or vagina.
- Use Clindamycin Phosphate Foam, 1% exactly as your doctor tells you to use it. See the “Instructions for Applying Clindamycin Phosphate Foam, 1%” below.
- Apply Clindamycin Phosphate Foam, 1% 1 time a day.
- Wash your skin with mild soap and water and dry before applying Clindamycin Phosphate Foam, 1%.
- Do not dispense Clindamycin Phosphate Foam, 1% directly onto your hands or face, because the foam will begin to melt on contact with warm skin.

- Wash your hands after applying Clindamycin Phosphate Foam, 1%.

Throw away any of the unused medicine that you dispensed out of the can.

What should I avoid while using Clindamycin Phosphate Foam, 1%?

- Clindamycin Phosphate Foam, 1% is flammable. Avoid fire, flames, or smoking during and right after you apply Clindamycin Phosphate Foam, 1% to your skin.
- Avoid getting Clindamycin Phosphate Foam, 1% in or near your eyes, mouth, lips, or broken skin. If you get Clindamycin Phosphate Foam, 1% in your eyes, mouth, on lips or broken skin, rinse well with water.

What are possible side effects with Clindamycin Phosphate Foam, 1%? Clindamycin Phosphate Foam, 1% can cause serious side effects including:

- Inflammation of the colon (colitis). Clindamycin can cause severe colitis that may lead to death. Stop using Clindamycin Phosphate Foam, 1% and call your doctor right away if you have severe watery diarrhea, or bloody diarrhea.

The most common side effects of Clindamycin Phosphate Foam, 1% include:

- Skin irritation. Clindamycin Phosphate Foam, 1% may cause skin irritation such as burning, itching, or dryness. Stop using Clindamycin Phosphate Foam, 1% and talk with your doctor if you develop excessive skin irritation.
- Headache.

Tell your doctor if you have any side effect that bothers you or that does not go away.

These are not all the side effects of Clindamycin Phosphate Foam, 1%. For more information, ask your doctor or pharmacist.

Call your doctor for medical advice about side effects. You may report side effects to FDA at 1-800-FDA-1088. You may report side effects to Perrigo at 1-866-634-9120.

How should I store Clindamycin Phosphate Foam, 1%?

- Store Clindamycin Phosphate Foam, 1% at room temperature between 68°F to 77°F (20°C to 25°C).
- Keep Clindamycin Phosphate Foam, 1% away from heat. Never throw the can into a fire, even if the can is empty.
- Do not store Clindamycin Phosphate Foam, 1% at temperatures above 120°F (49°C).
- Do not break through (puncture) the Clindamycin Phosphate Foam, 1% can.

Keep Clindamycin Phosphate Foam, 1% and all medicines out of the reach of children.

General information about the safe and effective use of Clindamycin Phosphate Foam, 1%:

Medicines are sometimes prescribed for purposes other than those listed in Patient Information. Do not use Clindamycin Phosphate Foam, 1% for a condition for which it was not prescribed. Do not give Clindamycin Phosphate Foam, 1% to other people, even if they have the same symptoms you have. It may harm them.

This leaflet summarizes the most important information about Clindamycin Phosphate Foam, 1%. If you would like more information, talk with your doctor. You can also ask your pharmacist or doctor for information about Clindamycin Phosphate Foam, 1% that is written for health professionals.

What are the ingredients in Clindamycin Phosphate Foam, 1%?

Active ingredient: clindamycin phosphate

Inactive ingredients: cetyl alcohol, ethanol (58%), polysorbate 60, propylene glycol, purified water, and stearyl alcohol. The can is pressurized with a hydrocarbon (propane/butane) propellant.

This Patient Information has been approved by the U.S. Food and Drug Administration.

Made in Israel

Manufactured by Perrigo

Yeruham, Israel

Distributed by Perrigo

Allegan, MI 49010

www.perrigo.com

Rev 08-19

4T500 RC J4

PACKAGE LABEL

Clindamycin Phosphate 1% Foam, #100